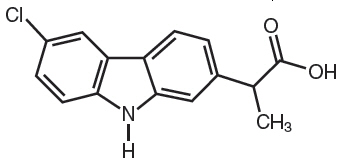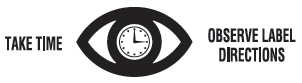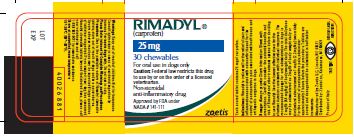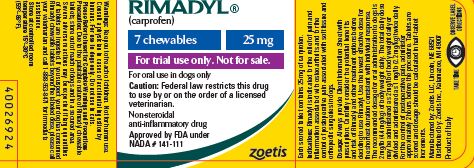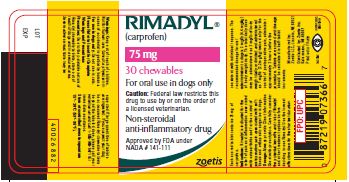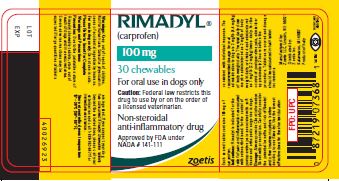 DRUG LABEL: RIMADYL
NDC: 54771-1504 | Form: TABLET, CHEWABLE
Manufacturer: Zoetis Inc.
Category: animal | Type: PRESCRIPTION ANIMAL DRUG LABEL
Date: 20240206

ACTIVE INGREDIENTS: carprofen 25 mg/1 1

RIMADYL®
(carprofen)

RIMADYL

(carprofen)

Chewable Tablets

Non-steroidal anti-inflammatory drug

For oral use in dogs only

CAUTION

Federal law restricts this drug to use by or on the order of a licensed veterinarian.

DESCRIPTION

Rimadyl (carprofen) is a non-steroidal anti-inflammatory drug (NSAID) of the propionic acid class that includes ibuprofen, naproxen, and ketoprofen. Carprofen is the nonproprietary designation for a substituted carbazole, 6-chloro-α-methyl-9H-carbazole-2-acetic acid. The empirical formula is C15H12ClNO2 and the molecular weight 273.72. The chemical structure of carprofen is:

Carprofen is a white, crystalline compound. It is freely soluble in ethanol, but practically insoluble in water at 25°C.

CLINICAL PHARMACOLOGY

Carprofen is a non-narcotic, non-steroidal anti-inflammatory agent with characteristic analgesic and antipyretic activity approximately equipotent to indomethacin in animal models.^1

The mechanism of action of carprofen, like that of other NSAIDs, is believed to be associated with the inhibition of cyclooxygenase activity. Two unique cyclooxygenases have been described in mammals.^2 The constitutive cyclooxygenase, COX-1, synthesizes prostaglandins necessary for normal gastrointestinal and renal function. The inducible cyclooxygenase, COX-2, generates prostaglandins involved in inflammation. Inhibition of COX-1 is thought to be associated with gastrointestinal and renal toxicity while inhibition of COX-2 provides anti-inflammatory activity. The specificity of a particular NSAID for COX-2 versus COX-1 may vary from species to species.^3 In an in vitro study using canine cell cultures, carprofen demonstrated selective inhibition of COX-2 versus COX-1.^4 Clinical relevance of these data has not been shown. Carprofen has also been shown to inhibit the release of several prostaglandins in two inflammatory cell systems: rat polymorphonuclear leukocytes (PMN) and human rheumatoid synovial cells, indicating inhibition of acute (PMN system) and chronic (synovial cell system) inflammatory reactions.^1

Several studies have demonstrated that carprofen has modulatory effects on both humoral and cellular immune responses.^5–9 Data also indicate that carprofen inhibits the production of osteoclast-activating factor (OAF), PGE1, and PGE2 by its inhibitory effect in prostaglandin biosynthesis.^1

Based upon comparison with data obtained from intravenous administration, carprofen is rapidly and nearly completely absorbed (more than 90% bioavailable) when administered orally.^10 Peak blood plasma concentrations are achieved in 1–3 hours after oral administration of 1, 5, and 25 mg/kg to dogs. The mean terminal half-life of carprofen is approximately 8 hours (range 4.5–9.8 hours) after single oral doses varying from 1–35 mg/kg of body weight. After a 100 mg single intravenous bolus dose, the mean elimination half-life was approximately 11.7 hours in the dog. Rimadyl is more than 99% bound to plasma protein and exhibits a very small volume of distribution.

Carprofen is eliminated in the dog primarily by biotransformation in the liver followed by rapid excretion of the resulting metabolites (the ester glucuronide of carprofen and the ether glucuronides of 2 phenolic metabolites, 7-hydroxy carprofen and 8-hydroxy carprofen) in the feces (70–80%) and urine (10–20%). Some enterohepatic circulation of the drug is observed.

INDICATIONS

Rimadyl is indicated for the relief of pain and inflammation associated with osteoarthritis and for the control of postoperative pain associated with soft tissue and orthopedic surgeries in dogs.

CONTRAINDICATIONS

Rimadyl should not be used in dogs exhibiting previous hypersensitivity to carprofen.

WARNINGS

Keep out of reach of children. Not for human use. Consult a physician in cases of accidental ingestion by humans. For use in dogs only. Do not use in cats.

All dogs should undergo a thorough history and physical examination before initiation of NSAID therapy.
Appropriate laboratory tests to establish hematological and serum biochemical baseline data prior to, and periodically during, administration of any NSAID should be considered. Owners should be advised to observe for signs of potential drug toxicity (see Information for Dog Owners, Adverse Reactions, Animal Safety and Post-Approval Experience).

PRECAUTIONS

As a class, cyclooxygenase inhibitory NSAIDs may be associated with gastrointestinal, renal and hepatic toxicity. Effects may result from decreased prostaglandin production and inhibition of the enzyme cyclooxygenase which is responsible for the formation of prostaglandins from arachidonic acid.^11–14 When NSAIDs inhibit prostaglandins that cause inflammation they may also inhibit those prostaglandins which maintain normal homeostatic function. These anti-prostaglandin effects may result in clinically significant disease in patients with underlying or pre-existing disease more often than in healthy patients.^12,14 NSAID therapy could unmask occult disease which has previously been undiagnosed due to the absence of apparent clinical signs. Patients with underlying renal disease for example, may experience exacerbation or decompensation of their renal disease while on NSAID therapy.^11–14 The use of parenteral fluids during surgery should be considered to reduce the potential risk of renal complications when using NSAIDs perioperatively.

Carprofen is an NSAID, and as with others in that class, adverse reactions may occur with its use. The most frequently reported effects have been gastrointestinal signs. Events involving suspected renal, hematologic, neurologic, dermatologic, and hepatic effects have also been reported. Patients at greatest risk for renal toxicity are those that are dehydrated, on concomitant diuretic therapy, or those with renal, cardiovascular, and/or hepatic dysfunction. Concurrent administration of potentially nephrotoxic drugs should be approached cautiously, with appropriate monitoring. Concomitant use of Rimadyl with other anti-inflammatory drugs, such as other NSAIDs or corticosteroids, should be avoided because of the potential increase of adverse reactions, including gastrointestinal ulcerations and/or perforations. Sensitivity to drug-associated adverse reactions varies with the individual patient. Dogs that have experienced adverse reactions from one NSAID may experience adverse reactions from another NSAID. Rimadyl treatment was not associated with renal toxicity or gastrointestinal ulceration in well-controlled safety studies of up to ten times the dose in healthy dogs.

Rimadyl is not recommended for use in dogs with bleeding disorders (e.g., Von Willebrand's disease), as safety has not been established in dogs with these disorders. The safe use of Rimadyl in animals less than 6 weeks of age, pregnant dogs, dogs used for breeding purposes, or in lactating bitches has not been established. Studies to determine the activity of Rimadyl when administered concomitantly with other protein-bound or similarly metabolized drugs have not been conducted. Drug compatibility should be monitored closely in patients requiring additional therapy. Such drugs commonly used include cardiac, anticonvulsant and behavioral medications. It has been suggested that treatment with carprofen may reduce the level of inhalant anesthetics needed.^15

If additional pain medication is warranted after administration of the total daily dose of Rimadyl, alternative analgesia should be considered. The use of another NSAID is not recommended. Consider appropriate washout times when switching from one NSAID to another or when switching from corticosteroids use to NSAID use.

Due to the palatable nature of Rimadyl chewable tablets, store out of reach of dogs in a secured location. Severe adverse reactions may occur if large quantities of tablets are ingested. If you suspect your dog has consumed Rimadyl chewable tablets above the labeled dose, please call your veterinarian for immediate assistance and notify Zoetis Inc. 1-888-963-8471.

INFORMATION FOR DOG OWNERS

Rimadyl, like other drugs of its class, is not free from adverse reactions. Owners should be advised of the potential for adverse reactions and be informed of the clinical signs associated with drug intolerance. Adverse reactions may include decreased appetite, vomiting, diarrhea, dark or tarry stools, increased water consumption, increased urination, pale gums due to anemia, yellowing of gums, skin or white of the eye due to jaundice, lethargy, incoordination, seizure, or behavioral changes. Serious adverse reactions associated with this drug class can occur without warning and in rare situations result in death (see Adverse Reactions). Owners should be advised to discontinue Rimadyl therapy and contact their veterinarian immediately if signs of intolerance are observed. The vast majority of patients with drug related adverse reactions have recovered when the signs are recognized, the drug is withdrawn, and veterinary care, if appropriate, is initiated. Owners should be advised of the importance of periodic follow up for all dogs during administration of any NSAID.

ADVERSE REACTIONS

During investigational studies for the caplet formulation with twice daily administration of 1 mg/lb, no clinically significant adverse reactions were reported. Some clinical signs were observed during field studies (n=297) which were similar for carprofen caplet- and placebo-treated dogs. Incidences of the following were observed in both groups: vomiting (4%), diarrhea (4%), changes in appetite (3%), lethargy (1.4%), behavioral changes (1%), and constipation (0.3%). The product vehicle served as control.

There were no serious adverse events reported during clinical field studies with once daily administration of 2 mg/lb. The following categories of abnormal health observations were reported. The product vehicle served as control.

Percentage of Dogs with Abnormal Health Observations Reported in Clinical Field Study (2 mg/lb once daily)
Observation | Rimadyl (n=129) | Placebo (n=132)
Inappetence | 1.6 | 1.5
Vomiting | 3.1 | 3.8
Diarrhea/Soft stool | 3.1 | 4.5
Behavior change | 0.8 | 0.8
Dermatitis | 0.8 | 0.8
PU/PD | 0.8 | —
SAP increase | 7.8 | 8.3
ALT increase | 5.4 | 4.5
AST increase | 2.3 | 0.8
BUN increase | 3.1 | 1.5
Bilirubinuria | 16.3 | 12.1
Ketonuria | 14.7 | 9.1

Clinical pathology parameters listed represent reports of increases from pre-treatment values; medical judgment is necessary to determine clinical relevance.

During investigational studies of surgical pain for the caplet formulation, no clinically significant adverse reactions were reported. The product vehicle served as control.

Percentage of Dogs with Abnormal Health Observations Reported in Surgical Pain Field Studies with Caplets (2 mg/lb once daily)
Observation [A single dog may have experienced more than one occurrence of an event.] | Rimadyl (n=148) | Placebo (n=149)
Vomiting | 10.1 | 13.4
Diarrhea/Soft stool | 6.1 | 6.0
Ocular disease | 2.7 | 0
Inappetence | 1.4 | 0
Dermatitis/Skin lesion | 2.0 | 1.3
Dysrhythmia | 0.7 | 0
Apnea | 1.4 | 0
Oral/Periodontal disease | 1.4 | 0
Pyrexia | 0.7 | 1.3
Urinary tract disease | 1.4 | 1.3
Wound drainage | 1.4 | 0

* A single dog may have experienced more than one occurrence of an event.
During investigational studies for the chewable tablet formulation, gastrointestinal signs were observed in some dogs. These signs included vomiting and soft stools.

Post-Approval Experience

Although not all adverse reactions are reported, the following adverse reactions are based on voluntary post-approval adverse drug experience reporting. The categories of adverse reactions are listed in decreasing order of frequency by body system.

Gastrointestinal: Vomiting, diarrhea, constipation, inappetence, melena, hematemesis, gastrointestinal ulceration, gastrointestinal bleeding, pancreatitis.

Hepatic: Inappetence, vomiting, jaundice, acute hepatic toxicity, hepatic enzyme elevation, abnormal liver function test(s), hyperbilirubinemia, bilirubinuria, hypoalbuminemia. Approximately one-fourth of hepatic reports were in Labrador Retrievers.

Neurologic: Ataxia, paresis, paralysis, seizures, vestibular signs, disorientation.

Urinary: Hematuria, polyuria, polydipsia, urinary incontinence, urinary tract infection, azotemia, acute renal failure, tubular abnormalities including acute tubular necrosis, renal tubular acidosis, glucosuria.

Behavioral: Sedation, lethargy, hyperactivity, restlessness, aggressiveness.

Hematologic: Immune-mediated hemolytic anemia, immune-mediated thrombocytopenia, blood loss anemia, epistaxis.

Dermatologic: Pruritus, increased shedding, alopecia, pyotraumatic moist dermatitis (hot spots), necrotizing panniculitis/vasculitis, ventral ecchymosis.

Immunologic or hypersensitivity: Facial swelling, hives, erythema.

In rare situations, death has been associated with some of the adverse reactions listed above.

To report a suspected adverse reaction call 1-888-963-8471.

DOSAGE AND ADMINISTRATION

Always provide Client Information Sheet with prescription. Carefully consider the potential benefits and risk of Rimadyl and other treatment options before deciding to use Rimadyl. Use the lowest effective dose for the shortest duration consistent with individual response. The recommended dosage for oral administration to dogs is 2 mg/lb of body weight daily. The total daily dose may be administered as 2 mg/lb of body weight once daily or divided and administered as 1 mg/lb twice daily. For the control of postoperative pain, administer approximately 2 hours before the procedure. Rimadyl chewable tablets are scored and dosage should be calculated in half-tablet increments. Tablets can be halved by placing the tablet on a hard surface and pressing down on both sides of the score. Rimadyl chewable tablets are palatable and willingly consumed by most dogs when offered by the owner. Therefore, they may be fed by hand or placed on food. Care should be taken to ensure that the dog consumes the complete dose.

PALATABILITY

A controlled palatability study was conducted which demonstrated that Rimadyl chewable tablets were readily accepted and consumed on first offering by a majority of dogs.

EFFECTIVENESS

Confirmation of the effectiveness of Rimadyl for the relief of pain and inflammation associated with osteoarthritis, and for the control of postoperative pain associated with soft tissue and orthopedic surgeries, was demonstrated in 5 placebo-controlled, masked studies examining the anti-inflammatory and analgesic effectiveness of Rimadyl caplets in various breeds of dogs.

Separate placebo-controlled, masked, multicenter field studies confirmed the anti-inflammatory and analgesic effectiveness of Rimadyl caplets when dosed at 2 mg/lb once daily or when divided and administered at 1 mg/lb twice daily. In these 2 field studies, dogs diagnosed with osteoarthritis showed statistically significant overall improvement based on lameness evaluations by the veterinarian and owner observations when administered Rimadyl at labeled doses.

Separate placebo-controlled, masked, multicenter field studies confirmed the effectiveness of Rimadyl caplets for the control of postoperative pain when dosed at 2 mg/lb once daily in various breeds of dogs. In these studies, dogs presented for ovariohysterectomy, cruciate repair and aural surgeries were administered Rimadyl preoperatively and for a maximum of 3 days (soft tissue) or 4 days (orthopedic) postoperatively. In general, dogs administered Rimadyl showed statistically significant reduction in pain scores compared to controls.

ANIMAL SAFETY

Laboratory studies in unanesthetized dogs and clinical field studies have demonstrated that Rimadyl is well tolerated in dogs after oral administration.

In target animal safety studies, Rimadyl was administered orally to healthy Beagle dogs at 1, 3, and 5 mg/lb twice daily (1, 3 and 5 times the recommended total daily dose) for 42 consecutive days with no significant adverse reactions. Serum albumin for a single female dog receiving 5 mg/lb twice daily decreased to 2.1 g/dL after 2 weeks of treatment, returned to the pre-treatment value (2.6 g/dL) after 4 weeks of treatment, and was 2.3 g/dL at the final 6-week evaluation. Over the 6-week treatment period, black or bloody stools were observed in 1 dog (1 incident) treated with 1 mg/lb twice daily and in 1 dog (2 incidents) treated with 3 mg/lb twice daily. Redness of the colonic mucosa was observed in 1 male that received 3 mg/lb twice daily.

Two of 8 dogs receiving 10 mg/lb orally twice daily (10 times the recommended total daily dose) for 14 days exhibited hypoalbuminemia. The mean albumin level in the dogs receiving this dose was lower (2.38 g/dL) than each of 2 placebo control groups (2.88 and 2.93 g/dL, respectively). Three incidents of black or bloody stool were observed in 1 dog. Five of 8 dogs exhibited reddened areas of duodenal mucosa on gross pathologic examination. Histologic exam of these areas revealed no evidence of ulceration, but did show minimal congestion of the lamina propria in 2 of the 5 dogs.

In separate safety studies lasting 13 and 52 weeks, respectively, dogs were administered orally up to 11.4 mg/lb/day (5.7 times the recommended total daily dose of 2 mg/lb) of carprofen. In both studies, the drug was well tolerated clinically by all of the animals. No gross or histologic changes were seen in any of the treated animals. In both studies, dogs receiving the highest doses had average increases in serum L-alanine aminotransferase (ALT) of approximately 20 IU.

In the 52-week study, minor dermatologic changes occurred in dogs in each of the treatment groups but not in the control dogs. The changes were described as slight redness or rash and were diagnosed as non-specific dermatitis. The possibility exists that these mild lesions were treatment related, but no dose relationship was observed.

Clinical field studies were conducted with 549 dogs of different breeds at the recommended oral doses for 14 days (297 dogs were included in a study evaluating 1 mg/lb twice daily and 252 dogs were included in a separate study evaluating 2 mg/lb once daily). In both studies the drug was clinically well tolerated and the incidence of clinical adverse reactions for Rimadyl-treated animals was no higher than placebo-treated animals (placebo contained inactive ingredients found in Rimadyl). For animals receiving 1 mg/lb twice daily, the mean post-treatment serum ALT values were 11 IU greater and 9 IU less than pre-treatment values for dogs receiving Rimadyl and placebo, respectively. Differences were not statistically significant. For animals receiving 2 mg/lb once daily, the mean post-treatment serum ALT values were 4.5 IU greater and 0.9 IU less than pre-treatment values for dogs receiving Rimadyl and placebo, respectively. In the latter study, 3 Rimadyl-treated dogs developed a 3-fold or greater increase in (ALT) and/or (AST) during the course of therapy. One placebo-treated dog had a greater than 2-fold increase in ALT. None of these animals showed clinical signs associated with laboratory value changes. Changes in the clinical laboratory values (hematology and clinical chemistry) were not considered clinically significant. The 1 mg/lb twice daily course of therapy was repeated as needed at 2-week intervals in 244 dogs, some for as long as 5 years.

Clinical field studies were conducted in 297 dogs of different breeds undergoing orthopedic or soft tissue surgery. Dogs were administered 2 mg/lb of Rimadyl two hours prior to surgery then once daily, as needed for 2 days (soft tissue surgery) or 3 days (orthopedic surgery). Rimadyl was well tolerated when used in conjunction with a variety of anesthetic-related drugs. The type and severity of abnormal health observation in Rimadyl- and placebo-treated animals were approximately equal and few in number (see Adverse Reactions). The most frequent abnormal health observation was vomiting and was observed at approximately the same frequency in Rimadyl- and placebo-treated animals. Changes in clinicopathologic indices of hematopoietic, renal, hepatic, and clotting function were not clinically significant. The mean post-treatment serum ALT values were 7.3 IU and 2.5 IU less than pre-treatment values for dogs receiving Rimadyl and placebo, respectively. The mean post-treatment AST values were 3.1 IU less for dogs receiving Rimadyl and 0.2 IU greater for dogs receiving placebo.

STORAGE

Store at controlled room temperature 15°–30°C (59°–86°F).

HOW SUPPLIED

Rimadyl chewable tablets are scored, and contain 25 mg, 75 mg, or 100 mg of carprofen per tablet. Each tablet size is packaged in bottles containing 7, 30, 60, or 180 tablets.

REFERENCES

1. Baruth H, et al: In Anti-Inflammatory and Anti-Rheumatic Drugs, Vol. II, Newer Anti-Inflammatory Drugs, Rainsford KD, ed. CRC Press, Boca Raton, p. 33, 1986.

2. Vane JR, Botting RM: Mechanism of action of anti-inflammatory drugs. Scand J Rheumatol 25:102, pp. 9–21.

3. Grossman CJ, Wiseman J, Lucas FS, et al: Inhibition of constitutive and inducible cyclooxygenase activity in human platelets and mononuclear cells by NSAIDs and Cox-2 inhibitors. Inflammation Research 44:253–257, 1995.

4. Ricketts AP, Lundy KM, Seibel SB: Evaluation of selective inhibition of canine cyclooxygenase 1 and 2 by carprofen and other nonsteroidal anti-inflammatory drugs. Am J Vet Res 59:11, pp. 1441–1446, November 1998.

5. Ceuppens JL, et al: Non-steroidal anti-inflammatory agents inhibit the synthesis of IgM rheumatoid factor in vitro. Lancet 1:528, 1982.

6. Ceuppens JL, et al: Endogenous prostaglandin E2 enhances polyclonal immunoglobulin production by ionically inhibiting T suppressor cell activity. Cell Immunol 70:41, 1982.

7. Schleimer RP, et al: The effects of prostaglandin synthesis inhibition on the immune response. Immunopharmacology 3:205, 1981.

8. Leung KH, et al: Modulation of the development of cell mediated immunity: Possible roles of the products of cyclooxygenase and lipoxygenase pathways of arachidonic acid metabolism. Int J Immunopharmacology 4:195, 1982.

9. Veit BC: Immunoregulatory activity of cultured-induced suppressor macrophages. Cell Immunol 72:14, 1982.

10. Schmitt M, et al: Biopharmaceutical evaluation of carprofen following single intravenous, oral, and rectal doses in dogs. Biopharm Drug Dispos 11(7):585, 1990.

11. Kore AM: Toxicology of nonsteroidal anti-inflammatory drugs. Veterinary Clinics of North America, Small Animal Practice 20, March 1990.

12. Binns SH: Pathogenesis and pathophysiology of ischemic injury in cases of acute renal failure. Compend for Cont Ed 16:1, January 1994.

13. Boothe DM: Prostaglandins: Physiology and clinical implications. Compend for Cont Ed 6:11, November 1984.

14. Rubin SI: Nonsteroidal anti-inflammatory drugs, prostaglandins, and the kidney. JAVMA 188:9, May 1986.

15. Ko CH, Lange DN, Mandsager RE, et al: Effects of butorphanol and carprofen on the minimal alveolar concentration of isoflurane in dogs. JAVMA 217:1025–1028, 2000.

For a copy of the Material Safety Data Sheet (MSDS) call 1-888-963-8471. To report adverse reactions call Zoetis Inc. 1-888-963-8471.

Approved by FDA under NADA # 141-111

zoetis

Manufactured by:
Zoetis LLC
Lincoln, NE 68521

Distributed by:
Zoetis Inc.
Kalamazoo, MI 49007

40026875

Revised: April 2019

Dog Owner Information about RIMADYL® Chewable Tablets (carprofen)

Rimadyl® (pronounced "Rim-a-dill") for Osteoarthritis and Post-Surgical Pain
Generic name: carprofen ("car-pro-fen")

This summary contains important information about Rimadyl. You should read this information before you start giving your dog Rimadyl and review it each time the prescription is refilled. This sheet is provided only as a summary and does not take the place of instructions from your veterinarian. Talk to your veterinarian if you do not understand any of this information or if you want to know more about Rimadyl.

What is Rimadyl?

Rimadyl is a nonsteroidal anti-inflammatory drug (NSAID) that is used to reduce pain and inflammation (soreness) due to osteoarthritis and pain following surgery in dogs. Rimadyl is a prescription drug for dogs. It is available as a caplet and chewable tablet and is given to dogs by mouth.

Osteoarthritis (OA) is a painful condition caused by "wear and tear" of cartilage and other parts of the joints that may result in the following changes or signs in your dog:

- Limping or lameness
- Decreased activity or exercise (reluctance to stand, climb stairs, jump or run, or difficulty in performing these activities)
- Stiffness or decreased movement of joints

To control surgical pain (e.g. for surgeries such as spays, ear procedures or orthopedic repairs) your veterinarian may administer Rimadyl before the procedure and recommend that your dog be treated for several days after going home.

What kind of results can I expect when my dog is on Rimadyl?

While Rimadyl is not a cure for osteoarthritis, it can relieve the pain and inflammation of OA and improve your dog's mobility.

- Response varies from dog to dog but can be quite dramatic.
- In most dogs, improvement can be seen in a matter of days.
- If Rimadyl is discontinued or not given as directed, your dog's pain and inflammation may come back.

Who should not take Rimadyl?

Your dog should not be given Rimadyl if he/she:

- Has had an allergic reaction to carprofen, the active ingredient of Rimadyl.
- Has had an allergic reaction to aspirin or other NSAIDs (for example deracoxib, etodolac, firocoxib, meloxicam, phenylbutazone or tepoxalin) such as hives, facial swelling, or red or itchy skin.

Rimadyl should be given to dogs only. Cats should not be given Rimadyl. Call your veterinarian immediately if your cat receives Rimadyl. People should not take Rimadyl. Keep Rimadyl and all medicines out of reach of children. Call your physician immediately if you accidentally take Rimadyl.

How to give Rimadyl to your dog.

Rimadyl should be given according to your veterinarian's instructions. Your veterinarian will tell you what amount of Rimadyl is right for your dog and for how long it should be given. Most dogs will take Rimadyl Chewable Tablets right out of your hand or the tablet can be placed in the mouth. Rimadyl may be given with or without food.

What to tell/ask your veterinarian before giving Rimadyl.

Talk to your veterinarian about:

- The signs of OA you have observed (for example limping, stiffness).
- The importance of weight control and exercise in the management of OA.
- What tests might be done before Rimadyl is prescribed.
- How often your dog may need to be examined by your veterinarian.
- The risks and benefits of using Rimadyl.

Tell your veterinarian if your dog has ever had the following medical problems:

- Experienced side effects from Rimadyl or other NSAIDs, such as aspirin
- Digestive upset (vomiting and/or diarrhea)
- Liver disease
- Kidney disease
- A bleeding disorder (for example, Von Willebrand's disease)

Tell your veterinarian about:

- Any other medical problems or allergies that your dog has now or has had.
- All medicines that you are giving your dog or plan to give your dog, including those you can get without a prescription.

Tell your veterinarian if your dog is:

- Pregnant, nursing or if you plan to breed your dog.

What are the possible side effects that may occur in my dog during Rimadyl therapy?

Rimadyl, like other drugs, may cause some side effects. Serious but rare side effects have been reported in dogs taking NSAIDs, including Rimadyl. Serious side effects can occur with or without warning and in rare situations result in death.

The most common NSAID-related side effects generally involve the stomach (such as bleeding ulcers), and liver or kidney problems. Look for the following side effects that can indicate your dog may be having a problem with Rimadyl or may have another medical problem:

- Decrease or increase in appetite
- Vomiting
- Change in bowel movements (such as diarrhea, or black, tarry or bloody stools)
- Change in behavior (such as decreased or increased activity level, incoordination, seizure or aggression)
- Yellowing of gums, skin, or whites of the eyes (jaundice)
- Change in drinking habits (frequency, amount consumed)
- Change in urination habits (frequency, color, or smell)
- Change in skin (redness, scabs, or scratching)

It is important to stop therapy and contact your veterinarian immediately if you think your dog has a medical problem or side effect from Rimadyl therapy. If you have additional questions about possible side effects, talk to your veterinarian.

Can Rimadyl be given with other medicines?

Rimadyl should not be given with other NSAIDs (for example, aspirin, deracoxib, etodolac, firocoxib, meloxicam, tepoxalin) or steroids (for example, cortisone, dexamethasone, prednisone, triamcinolone).

Tell your veterinarian about all medicines you have given your dog in the past, and any medicines that you are planning to give with Rimadyl. This should include other medicines that you can get without a prescription. Your veterinarian may want to check that all of your dog's medicines can be given together.

What do I do in case my dog eats more than the prescribed amount of Rimadyl?

Contact your veterinarian immediately if your dog eats more than the prescribed amount of Rimadyl.

How to store Rimadyl Chewable Tablets.

Rimadyl Chewable Tablets are designed to taste good to animals.

Keep Rimadyl Chewable Tablets in a secured storage area out of the reach of your dog and other pets. If your dog ingests more than your veterinarian prescribed, or if your other pets take Rimadyl Chewable Tablets, contact your veterinarian right away.

What else should I know about Rimadyl?

This sheet provides a summary of information about Rimadyl. If you have any questions or concerns about Rimadyl or osteoarthritis pain, or postoperative pain, talk to your veterinarian.

As with all prescribed medicines, Rimadyl should only be given to the dog for which it was prescribed. It should be given to your dog only for the condition for which it was prescribed.

It is important to periodically discuss your dog's response to Rimadyl at regular check ups. Your veterinarian will best determine if your dog is responding as expected and if your dog should continue receiving Rimadyl.

To report a suspected adverse reaction call Zoetis at 1-888-963-8471.

Manufactured by:
Zoetis LLC
Lincoln, NE 68521
Distributed by:
Zoetis Inc.
Kalamazoo, MI 49007

www.rimadyl.com

40026875

PRINCIPAL DISPLAY PANEL - 25 mg Tablet Bottle Label

Note: Each tablet size is packaged in bottles containing 7, 30, 60, or 180 tablets.

PRINCIPAL DISPLAY PANEL - 75 mg Tablet Bottle Label

Note: Each tablet size is packaged in bottles containing 7, 30, 60, or 180 tablets.

PRINCIPAL DISPLAY PANEL - 100 mg Tablet Bottle Label

Note: Each tablet size is packaged in bottles containing 7, 30, 60, or 180 tablets.